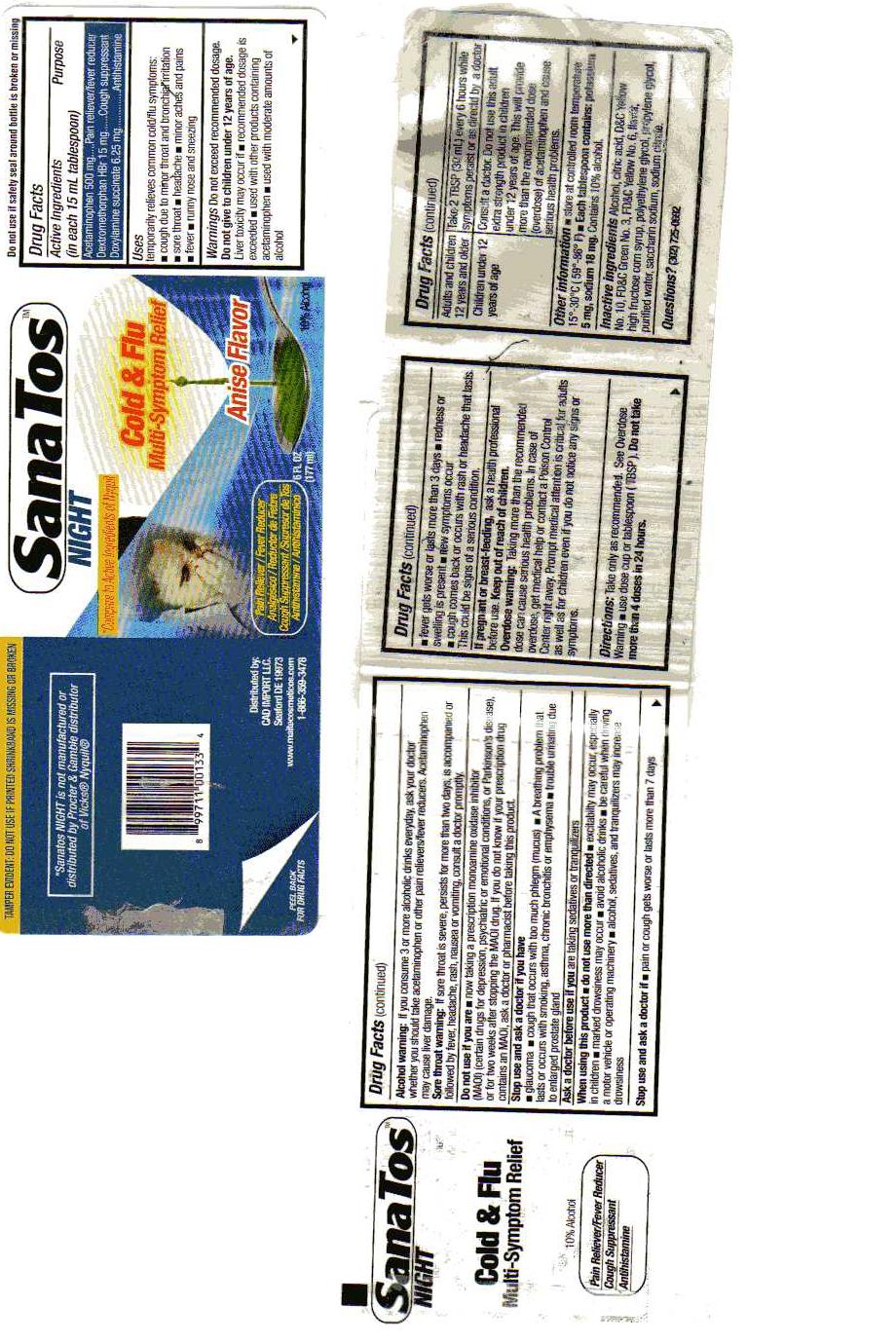 DRUG LABEL: Sanatos
NDC: 14505-399 | Form: LIQUID
Manufacturer: Pharmalab Enterprises Inc
Category: otc | Type: HUMAN OTC DRUG LABEL
Date: 20100909

ACTIVE INGREDIENTS: ACETAMINOPHEN 500 mg/15 mL; DEXTROMETHORPHAN HYDROBROMIDE 15 mg/15 mL; DOXYLAMINE SUCCINATE 6.25 mg/15 mL
INACTIVE INGREDIENTS: CITRIC ACID MONOHYDRATE; FD&C YELLOW NO. 6; PROPYLENE GLYCOL; WATER; SACCHARIN SODIUM; SODIUM CHLORIDE; SODIUM CITRATE; ALCOHOL; D&C YELLOW NO. 10; FD&C GREEN NO. 3; HIGH FRUCTOSE CORN SYRUP; PROPYLENE GLYCOL

Drug Facts

Active Ingredients Purpose
(in each 15 mL tablespoon)
Acetaminophen 500mg........ Pain Reliever/Fever Reducer
Dextromethorphan HBr 15mg...... Cough Suppressant
Doxylamine succinate 6.25mg..................Antihistamine

PURPOSE

Uses: temporarily relieves common cold/flu symptoms:

- Cough due to Minor Throat and Bronchial Irritation
- Sore Throat
- Headache
- Minor Aches and Pains
- Fever
- runny nose and sneezing

Warnings: Do not exceed recommended dosage.
Do not give to children under 12 years of age.
Liver Toxicity may occur if:

- Recommended dosage is exceeded
- Used with other products containing acetaminophen
- Used with moderate amounts of alcohol

Alcohol Warning: If you consume 3 or more alcoholic drinks, ask your doctor whether you should take acetaminophen or other pain relievers. Acetaminophen may cause liver damage.
Sore Throat Warning: If sore throat is severe, persists for more than two days, is accompanied or followed by fever, headache, rash, nausea or vomiting, consult a doctor promptly.

Do not use if you are:

- now taking a prescription monoamine oxidase inhibitor(MAOI) (certain drugs for depression, psychiatric or emotional conditions, or Parkinson's disease), or for two weeks after stopping the MAOI drug. If you do not know if your prescription drug contains an MAOI, ask a doctor or pharmacist before taking this product

Stop Use and ask a doctor if you have:

- Glaucoma
- Trouble urinating due to enlarged prostate gland
- Cough that occurs with too much phlegm(mucus)
- Persistent or chronic cough as occurs with smoking, asthma or emphysema
- Ask a doctor before use if you are taking sedatives or tranquilizers

Ask a doctor before use if you are taking sedatives or tranquilizers.

When using this product, do not use more than directed

- Excitability may occur, especially in children
- marked drowsiness may occur
- avoid alcoholic drinks
- be careful when driving a motor vehicle or operating machinery
- alcohol, sedatives, and tranquilizers may increase drowsiness

Stop Use and ask a doctor if:

- Pain or cough gets worse or lasts more than 7 days
- fever gets worse or lasts more than 3 days
- redness or swelling is present
- new symptoms occur
- cough comes back, or occurs with rash or headache that lasts. This could be signs of a serious condition.

PREGNANCY OR BREAST FEEDING

If pregnant of breast-feeding, ask a health professional before use.

Keep out of reach of children.

OVERDOSAGE

Overdose warning: Taking more than the recommended dose can cause serious health problems. In case of overdose, get medical help or contact a Poison Control Center right away. Prompt medical attention is critical for adults as well as for children even if you do not notice any signs or symptoms.

DOSAGE AND ADMINISTRATION

Directions: Take only as recommended. See Overdose Warning.

- use dose cup or tablespoon(TBSP). Do not use more than 4 doses in 24 hours

Adults and children 12 years and older: Take 2 TBSP(30ml) every 6 hours, while symptoms persist or as directed by a doctor

Children under 12 years of age: Consult a doctor. Do not use this adult extra strength product in children under 12 years of age. This will provide more than the recommended dose(overdose) of acetaminophen and cause serious problems.

Other information:

- Store at controlled room temperature 15-30 C (59-86F)
- each tablespoon contains: potassium 5 mg, sodium 18 mg. Contains 10% alcohol.

Questions? (302) 725-0692